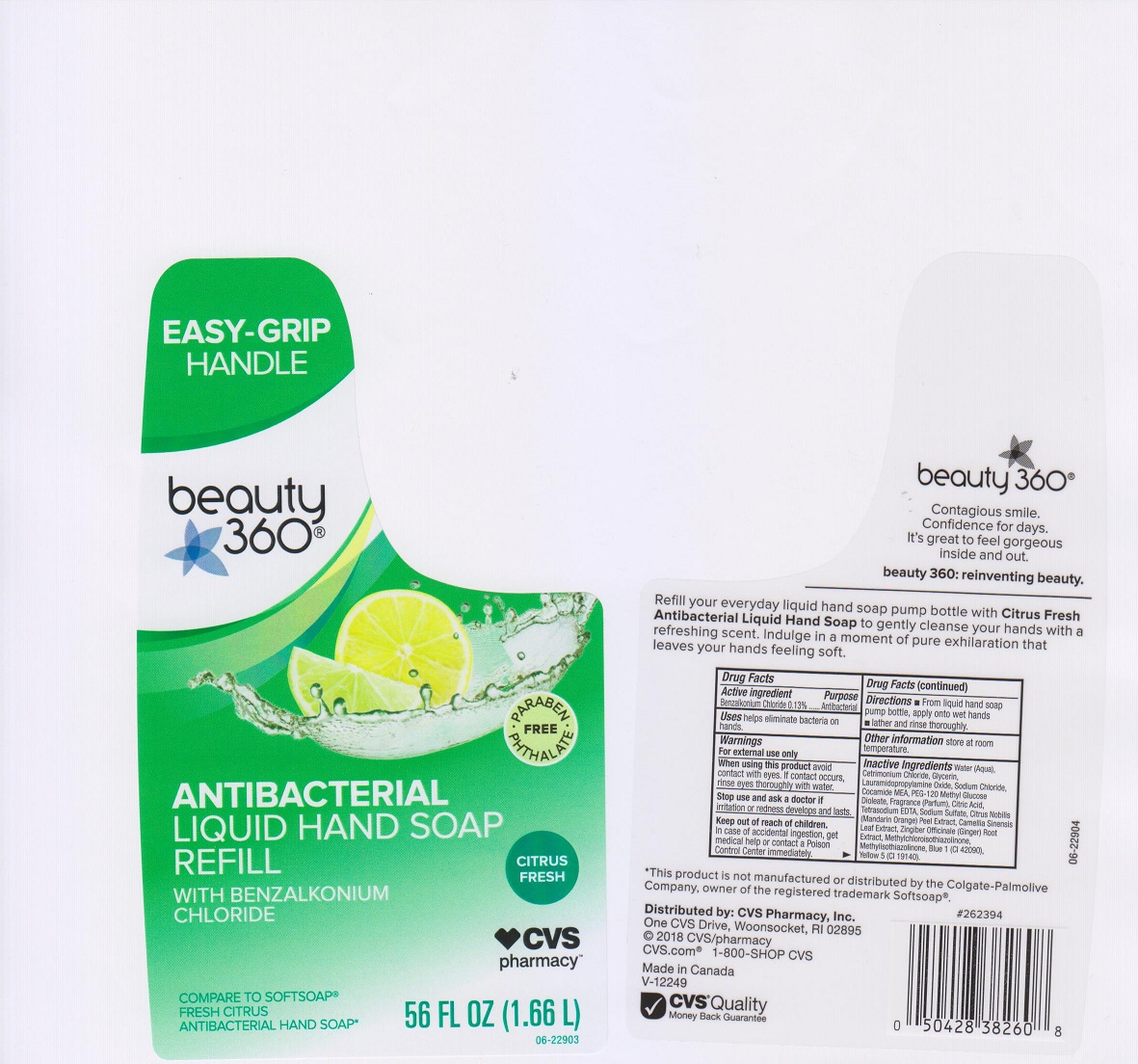 DRUG LABEL: CVS PHARMACY
NDC: 59779-724 | Form: LIQUID
Manufacturer: CVS PHARMACY
Category: otc | Type: HUMAN OTC DRUG LABEL
Date: 20200318

ACTIVE INGREDIENTS: BENZALKONIUM CHLORIDE 1.3 mg/1 mL
INACTIVE INGREDIENTS: FD&C BLUE NO. 1; GREEN TEA LEAF; CETRIMONIUM CHLORIDE; CITRIC ACID MONOHYDRATE; TANGERINE PEEL; COCO MONOETHANOLAMIDE; GLYCERIN; LAURAMIDOPROPYLAMINE OXIDE; METHYLCHLOROISOTHIAZOLINONE; METHYLISOTHIAZOLINONE; PEG-120 METHYL GLUCOSE DIOLEATE; SODIUM CHLORIDE; SODIUM SULFATE; EDETATE SODIUM; WATER; FD&C YELLOW NO. 5; GINGER

DRUG FACTS

Active ingredient

Benzalkonium Chloride 0.13%

Purpose

Antibacterial

Uses

helps eliminate bacteria on hands

Warnings

For external use only.

When using thhis product

avoid contact with eyes. If contact occurs, rinse eyes thoroughly with water.

Stop use and ask a doctor if

irritation or redness develops and lasts.

Keep out of reach of children.

In case of accidental ingestion, get medical help or contact a Poison Control Center immediately.

Directions

- apply onto wet hands
- lather and rinse thoroughly

Other information

store at room temperature

Inactive ingredients

Water (Aqua), Cetrimonium Chloride, Glycerin, Lauramidopropylamine Oxide, Sodium Chloride, Cocamide MEA, PEG-120 Methyl Glucose Dioleate, Fragrance (Parfum), Citric Acid, Tetrasodium EDTA, Sodium Sulfate, Citrus Nobilis (Mandarin Orange) Peel Extract, Camellia Sinensis Leaf Extract, Zingiber Officinanle (Ginger) Root Extract, Methylchloroisothiazolinone, Methylisothiazolinone, Blue 1 (CI 42090), Yellow 5 (CI 19140).